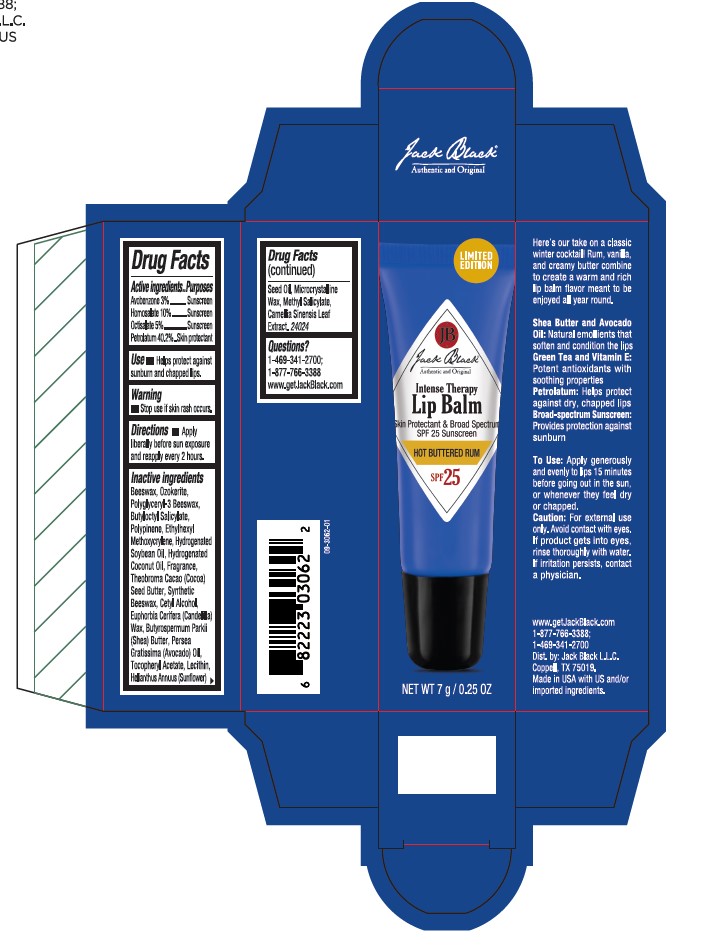 DRUG LABEL: Jack Black L.L.C.
NDC: 66738-221 | Form: OINTMENT
Manufacturer: Jack Black L.L.C.
Category: otc | Type: HUMAN OTC DRUG LABEL
Date: 20250905

ACTIVE INGREDIENTS: AVOBENZONE 3 g/100 mL; PETROLATUM 40.2 g/100 mL; OCTISALATE 5 g/100 mL; HOMOSALATE 10 g/100 mL
INACTIVE INGREDIENTS: HYDROGENATED COCONUT OIL; .ALPHA.-TOCOPHEROL ACETATE; BUTYLOCTYL SALICYLATE; CAMELLIA SINENSIS LEAF; BEESWAX; POLYGLYCERYL-3 BEESWAX; EUPHORBIA CERIFERA (CANDELILLA) WAX; METHYL SALICYLATE; MICROCRYSTALLINE WAX; CETYL ALCOHOL; SYNTHETIC BEESWAX; CERESIN; THEOBROMA CACAO (COCOA) SEED BUTTER; BUTYROSPERMUM PARKII (SHEA) BUTTER; ETHYLHEXYL METHOXYCRYLENE; HYDROGENATED SOYBEAN OIL; HELIANTHUS ANNUUS (SUNFLOWER) SEED OIL; PERSEA GRATISSIMA (AVOCADO) OIL

ACTIVE INGREDIENT

Avobenzone 3%
Homosalate 10%
Octisalate 5%
Petrolatum 40.2%

Purposes

Sunscreen

Sunscreen

Sunscreen

Skin protectant

Use

• Helps protect against sunburn and chapped lips

Warnings

Stop use if skin rash occurs.

Keep out of reach of children.

Directions

• Apply liberally before sun exposure and reapply every 2 hours.

Inactive ingredients

Beeswax, Ozokerite, Polyglyceryl-3 Beeswax, Butyloctyl Salicylate, Polypinene, Ethylhexyl Methoxycrylene, Hydrogenated Soybean Oil, Hydrogenated Coconut Oil, Fragrance, Theobroma Cacao (Cocoa) Seed Butter, Synthetic Beeswax, Cetyl Alcohol, Euphorbia Cerifera (Candelilla) Wax, Butyrospermum Parkii (Shea) Butter, Persea Gratissima (Avocado) Oil, Tocopheryl Acetate, Lecithin, Helianthus Annuus (Sunflower) Seed Oil, Microcrystalline Wax, Methyl Salicylate, Camellia Sinensis Leaf Extract.

Questions?

1-469-341-2700; 1-877-766-3388 www.getJackBlack.com